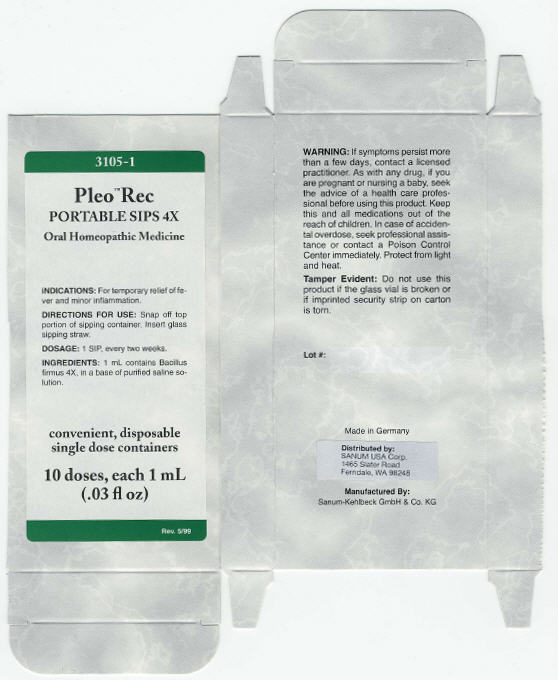 DRUG LABEL: Pleo Rec
NDC: 60681-3105 | Form: LIQUID
Manufacturer: Sanum Kehlbeck GmbH & Co. KG
Category: homeopathic | Type: HUMAN OTC DRUG LABEL
Date: 20091109

ACTIVE INGREDIENTS: bacillus firmus 4 [hp_X]/1 mL
INACTIVE INGREDIENTS: water; sodium chloride

Pleo™ Rec
PORTABLE SIPS 4X

Oral Homeopathic Medicine

10 doses, each 1 mL
(.03 fl oz)

INDICATIONS

For temporary relief of fever and minor inflammation.

DIRECTIONS FOR USE

Snap off top portion of sipping container. Insert glass sipping straw.

DOSAGE

1 SlP, every two weeks.

INGREDIENTS

1 mL contains Bacillus firmus 4X, in a base of purified saline solution.

WARNING

If symptoms persist more than a few days, contact a licensed practitioner. As with any drug, if you are pregnant or nursing a baby, seek the advice of a health care professional before using this product.

KEEP OUT OF REACH OF CHILDREN

Keep this and all medications out of the reach of children. In case of accidental overdose, seek professional assistance or contact a Poison Control Center immediately.

STORAGE AND HANDLING

Protect from light and heat.

Tamper Evident

Do not use this product if the glass vial is broken or if imprinted security strip on carton is torn.

Made in Germany

Distributed by:
SANUM USA Corp.
1465 Slater Road
Ferndale, WA 98248

Manufactured By:
Sanum-Kehlbeck GmbH & Co. KG

Rev. 5/99

PRINCIPAL DISPLAY PANEL - 1 mL Label

3105-1

Pleo™ Rec
PORTABLE SIPS 4X

OraI Homeopathic Medicine

INDICATIONS: For temporary relief of fe-
ver and minor inflammation.

DIRECTIONS FOR USE: Snap off top
portion of sipping container. Insert glass
sipping straw.

DOSAGE: 1 SlP, every two weeks.

INGREDIENTS: 1 mL contains Bacillus
firmus 4X, in a base of purified saline so-
lution.

convenient, disposable
single dose containers

10 doses, each 1 mL
(.03 fl oz)

Rev. 5/99